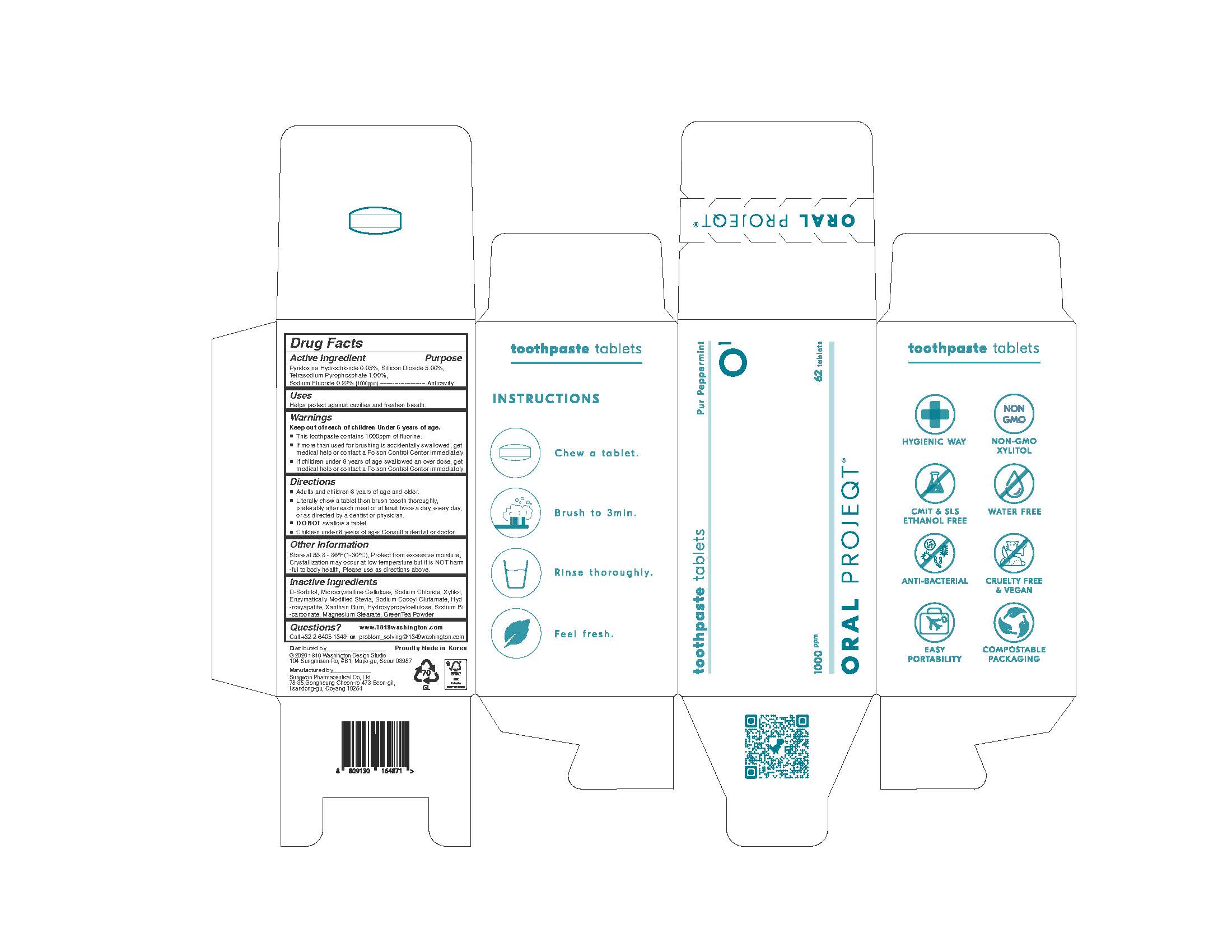 DRUG LABEL: ORAL PROJEQT O1 TOOTHPASTETABLETS
NDC: 76058-500 | Form: TABLET
Manufacturer: Sungwon Pharmaceutical Co., Ltd.
Category: otc | Type: HUMAN OTC DRUG LABEL
Date: 20220822

ACTIVE INGREDIENTS: SODIUM FLUORIDE 0.22 g/1 1; SILICON DIOXIDE 5 g/1 1; SODIUM PYROPHOSPHATE 1 g/1 1; PYRIDOXINE HYDROCHLORIDE 0.05 g/1 1
INACTIVE INGREDIENTS: XYLITOL; SORBITOL

ACTIVE INGREDIENT

Silicon Dioxide, Tetrasodium Pyrophosphate, Pyridoxine Hydrochloride, Sodium Fluoride

INACTIVE INGREDIENT

D-Sorbitol, Microcrystalline Cellulose, Sodium Chloride, Xylitol, Enzymatically Modified Stevia, Sodium Cocoyl Glutamate, GreenTea Flavor Powder, Combined Flavor(Coolmint Flavor Powder), Combined Flavor(Peppermint Flavor Powder), L-Menthol, Lemon Juice, Aloe Extract Powder, Tea Extract, Hydroxyapatite, Xanthan Gum, Hydroxypropylcellulose, Sodium Bicarbonate, Magnesium Stearate

PURPOSE

Helps protect against cavities and freshen breath.

KEEP OUT OF REACH OF CHILDREN

WARNING

Keep out of reach of children Under 6 years of age.
If more than used for brushing is accidentally swallowed, get
medical help or contact a Poison Control Center immediately.
This toothpaste contains 1000ppm of fluorine.
If children under 6 years of age swallowed an over dose, get
medical help or contact a Poison Control Center immediately.

USES

for oral use only

INDICATION & USAGE SECTION

Adults and children 6 years of age and older

Literally chew a tablet then brush teeeth thoroughly,
preferably after each meal or at least twice a day, every day,
or as directed by a dentist or physician.
DO NOT swallow a tablet.
Children under 6 years of age: Consult a dentist or doctor.